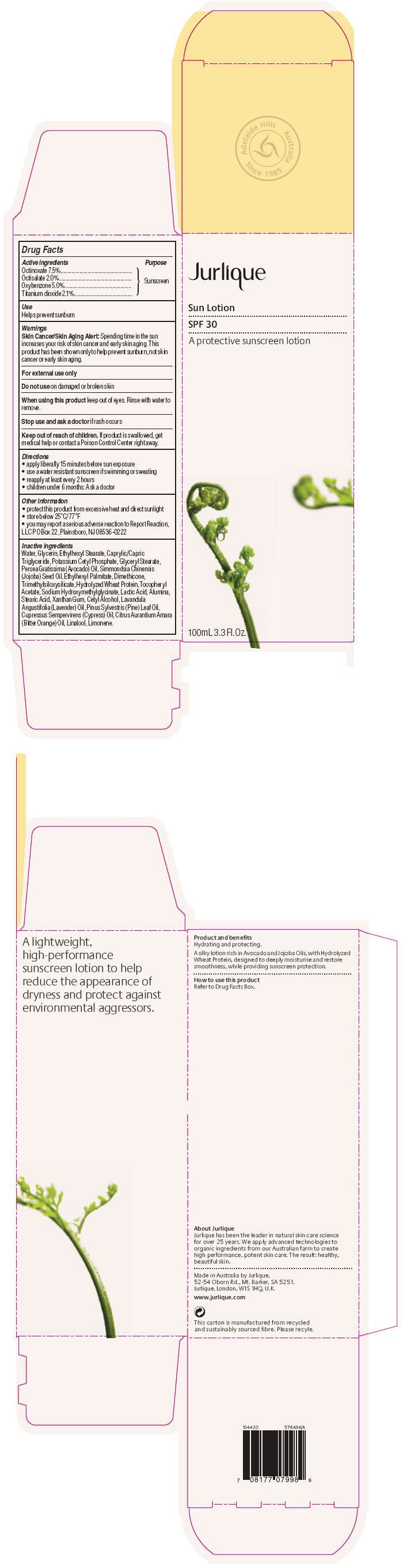 DRUG LABEL: Jurlique Sun Sunscreen SPF 30
NDC: 68105-005 | Form: CREAM, AUGMENTED
Manufacturer: Jurlique International Pty. Ltd.
Category: otc | Type: HUMAN OTC DRUG LABEL
Date: 20121121

ACTIVE INGREDIENTS: Octinoxate 75 mg/1 mL; Octisalate 20 mg/1 mL; Oxybenzone 50 mg/1 mL; Titanium Dioxide 21 mg/1 mL
INACTIVE INGREDIENTS: Water; Glycerin; Ethylhexyl Stearate; MEDIUM-CHAIN TRIGLYCERIDES; Potassium Cetyl Phosphate; GLYCERYL MONOSTEARATE; AVOCADO OIL; JOJOBA OIL; Ethylhexyl Palmitate; Dimethicone; HYDROLYZED WHEAT PROTEIN (ENZYMATIC, 3000 MW); .ALPHA.-TOCOPHEROL ACETATE; Sodium Hydroxymethylglycinate; Lactic Acid; Aluminum Oxide; Stearic Acid; Xanthan Gum; Cetyl Alcohol; LAVENDER OIL; PINE NEEDLE OIL (PINUS SYLVESTRIS); BITTER ORANGE OIL; LINALOOL, (+/-)-; LIMONENE, (+/-)-

Jurlique Sun Lotion Sunscreen SPF 30

Drug Facts

Active ingredients

Octinoxate 7.5%
Octisalate 2.0%
Oxybenzone 5.0%
Titanium dioxide 2.1%

Purpose

Sunscreen

Use

Helps prevent sunburn

Warnings

Skin Cancer/Skin Aging Alert

Spending time in the sun increases your risk of skin cancer and early skin aging. This product has been shown only to help prevent sunburn, not skin cancer or early skin aging.

For external use only

Do not use on damaged or broken skin

When using this product keep out of eyes. Rinse with water to remove.

Stop use and ask a doctor if rash occurs

Keep out of reach of children. If product is swallowed, get medical help or contact a Poison Control Center right away.

Directions

- apply liberally 15 minutes before sun exposure
- use a water resistant sunscreen if swimming or sweating
- reapply at least every 2 hours
- children under 6 months: Ask a doctor

Other information

- protect this product from excessive heat and direct sunlight
- store below 25°C/77°F
- you may report a serious adverse reaction to Report Reaction, LLC PO Box 22, Plainsboro, NJ 08536-0222

Inactive ingredients

Water, Glycerin, Ethylhexyl Stearate, Caprylic/Capric Triglyceride, Potassium Cetyl Phosphate, Glyceryl Stearate, Persea Gratissima (Avocado) Oil, Simmondsia Chinensis (Jojoba) Seed Oil, Ethylhexyl Palmitate, Dimethicone, Trimethylsiloxysilicate, Hydrolyzed Wheat Protein, Tocopheryl Acetate, Sodium Hydroxymethylglycinate, Lactic Acid, Alumina, Stearic Acid, Xanthan Gum, Cetyl Alcohol, Lavandula Angustifolia (Lavender) Oil, Pinus Sylvestris (Pine) Leaf Oil, Cupressus Sempervirens (Cypress) Oil, Citrus Aurantium Amara (Bitter Orange) Oil, Linalool, Limonene.

PRINCIPAL DISPLAY PANEL - 100mL Bottle Carton

Jurlique

Sun Lotion

SPF 30

A protective sunscreen lotion

100mL 3.3 Fl. Oz.